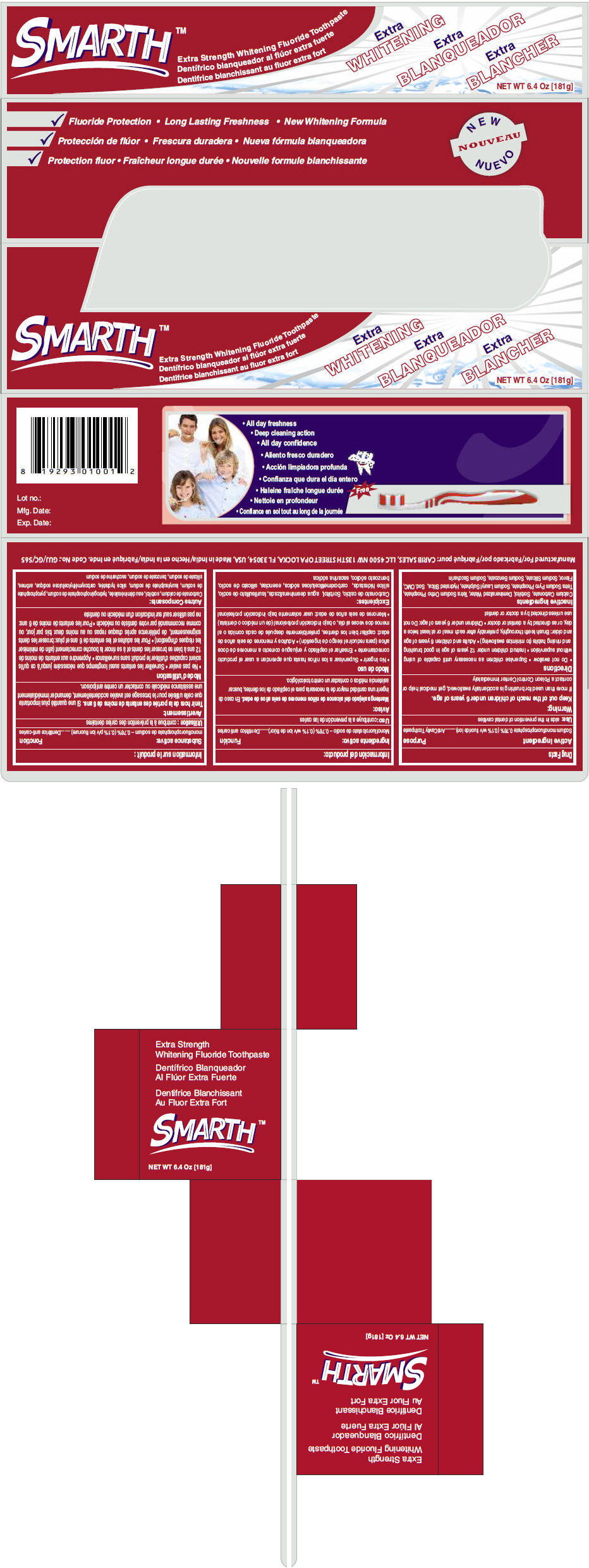 DRUG LABEL: Smarth 
NDC: 60927-118 | Form: PASTE, DENTIFRICE
Manufacturer: Carib Sales, LLC
Category: otc | Type: HUMAN OTC DRUG LABEL
Date: 20131008

ACTIVE INGREDIENTS: Sodium monofluorophosphate 7.6 mg/1 g
INACTIVE INGREDIENTS: Calcium Carbonate; Sorbitol; Water; Sodium Pyrophosphate; Sodium Lauryl Sulfate; Hydrated Silica; Sodium Silicate; Sodium Benzoate; Saccharin Sodium

Smarth™
Extra Strength Whitening

Drug Facts

Active ingredient

Sodium monofluorophosphate 0.76% (0.1% w/v fluoride ion)

Purpose

AntiCavity Toothpaste

Use

aids in the prevention of dental cavities

Warning

KEEP OUT OF REACH OF CHILDREN

Keep out of the reach of children under 6 years of age.

If more than used for brushing is accidentally swallowed, get medical help or contact a Poison Control Center immediately

Directions

- Do not swallow
- Supervise children as necessary until capable of using without supervision
- Instruct children under 12 years of age in good brushing and rinsing habits (to minimize swallowing)
- Adults and children 6 years of age and older: Brush teeth thoroughly, preferably after each meal or at least twice a day, or as directed by a dentist or doctor
- Children under 6 years of age: Do not use unless directed by a doctor or dentist

Inactive Ingredients

Calcium Carbonate, Sorbitol, Demineralized Water, Tetra Sodium Ortho Phosphate, Tetra Sodium Pyro Phosphate, Sodium Lauryl Sulphate, Hydrated Silica, Sod. CMC, Flavor, Sodium Silicate, Sodium Benzoate, Sodium Saccharin

PRINCIPAL DISPLAY PANEL - 181g Tube Carton

SMARTH™

Extra Strength Whitening Fluoride Toothpaste

Extra
WHITENING

NET WT 6.4 Oz [181g]